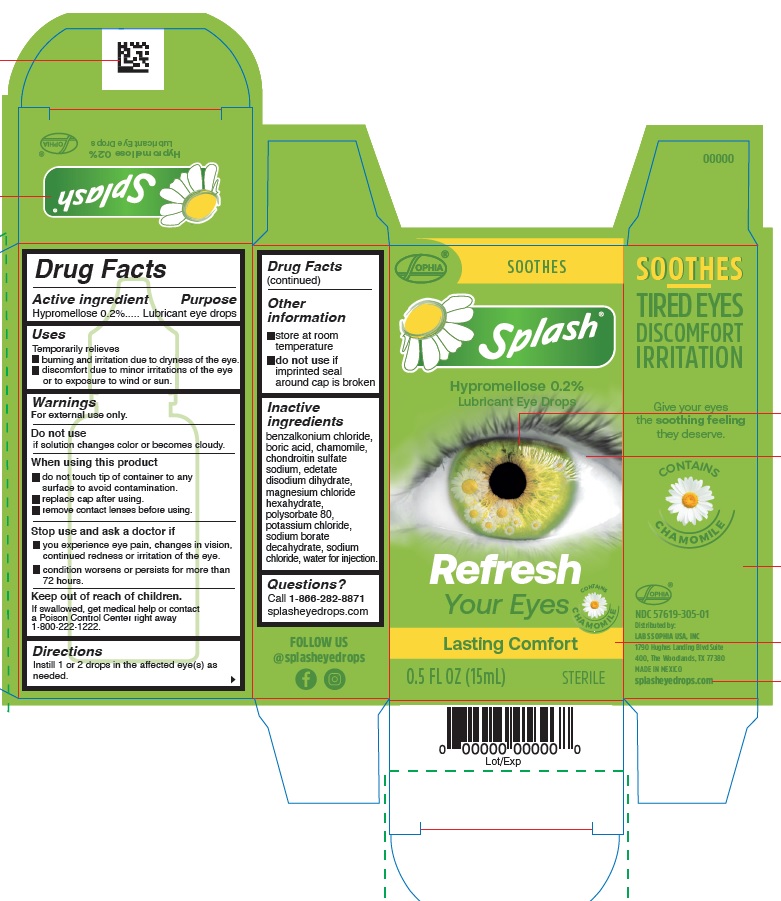 DRUG LABEL: Splash Refresh
NDC: 57619-305 | Form: SOLUTION/ DROPS
Manufacturer: LABORATORIOS SOPHIA, S.A. DE C.V.
Category: otc | Type: HUMAN OTC DRUG LABEL
Date: 20250902

ACTIVE INGREDIENTS: HYPROMELLOSE 2910 (4000 MPA.S) 0.2 g/100 mL
INACTIVE INGREDIENTS: BENZALKONIUM CHLORIDE; CHONDROITIN SULFATE (BOVINE); EDETATE DISODIUM; POLYSORBATE 80; WATER; MAGNESIUM CHLORIDE; SODIUM BORATE; SODIUM CHLORIDE; POTASSIUM CHLORIDE; BORIC ACID; CHAMOMILE

Splash Refresh

Drug Facts

Active ingredient

Hypromellose 0.2%

Purpose

Lubricant eye drops

Uses

Temporarily relieves

- burning and irritation due to dryness of the eye.
- discomfort due to minor irritations of the eye or to exposure to wind or sun.

Warnings

For external use only.

Do not use if solution changes color or becomes cloudy.

When using this product

- do not touch tip of container to any surface to avoid contamination.
- replace cap after using.
- remove contact lenses before using.

Stop use and ask a doctor if

- you experience eye pain, changes in vision, continued redness or irritation of the eye.
- condition worsens or persists for more than 72 hours.

Keep out of reach of children. If swallowed, get medical help or contact a Poison Control Center right away 1-800-222-1222.

Directions

instill 1 or 2 drops in the affected eye(s) as needed

Other information

- store at room temperature
- do not use if imprinted seal around cap is broken.

Inactive ingredients

benzalkonium chloride, boric acid, chamomile, chondroitin sulfate sodium, edetate disodium dihydrate, magnesium chloride hexahydrate, polysorbate 80, potassium chloride, sodium borate decahydrate, sodium chloride, water for injection.

Questions?

Call 1-866-282-8871

splasheyedrops.com

NDC 57619-305-01

Distributed by:

LABS SOPHIA USA, INC.

1790 Hughes Landing Blvd Suite 400

The Woodlands, TX 77380

MADE IN MEXICO

splasheyedrops.com

PACKAGE LABEL

SOPHIA®

Splash®

SOOTHES

Hypromellose 0.2%
Lubricant Eye Drops

Refresh Your Eyes

CONTAINS CHAMOMILE

Lasting Comfort

0.5 FL OZ (15mL) STERILE